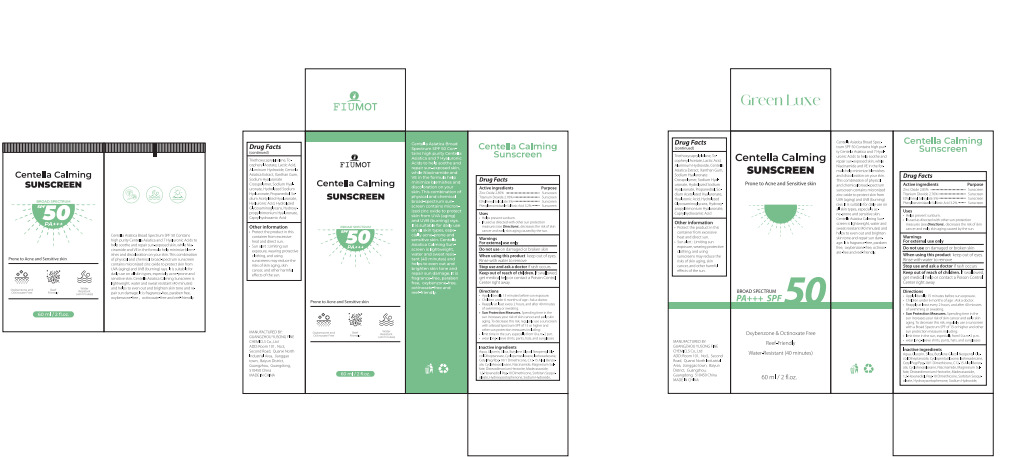 DRUG LABEL: Centella Calming SUNSCREEN
NDC: 84558-007 | Form: CREAM
Manufacturer: GUANGZHOU YUSONG FINE CHEMICLS Co., Ltd
Category: otc | Type: HUMAN OTC DRUG LABEL
Date: 20250209

ACTIVE INGREDIENTS: TITANIUM DIOXIDE 2.76 g/100 mL; ETHYLHEXYL SALICYLATE 5 g/100 mL; PHENYLBENZIMIDAZOLE SULFONIC ACID 3.2 g/100 mL; ZINC OXIDE 2.85 g/100 mL
INACTIVE INGREDIENTS: ALUMINUM HYDROXIDE; SORBITAN SESQUIOLEATE; PROPANEDIOL; PEG-9 DIGLYCIDYL ETHER/SODIUM HYALURONATE CROSSPOLYMER; XANTHAN GUM; SODIUM HYALURONATE; CAPRYLHYDROXAMIC ACID; SODIUM S-(2-HYDROXY-3-(3-(TRIHYDROXYSILYL)PROPOXY)PROPYL) SULFUROTHIOATE; TRIETHOXYCAPRYLYLSILANE; ALPHA-TOCOPHEROL ACETATE; LACTIC ACID; CENTELLA ASIATICA TRITERPENOIDS; HYDROLYZED CASEIN (ENZYMATIC; 1000 MW); SODIUM ACETYLATED HYALURONATE; HYALURONIC ACID; AQUA; GLYCERIN; SILICA; BUTYLENE GLYCOL; NEOPENTYL GLYCOL DIHEPTANOATE; CYCLOPENTASILOXANE; ISOHEXADECANE; CETYL PEG/PPG-10/1 DIMETHICONE (HLB 4); C12-15 ALKYL BENZOATE; CYCLOHEXASILOXANE; NIACINAMIDE; MAGNESIUM SULFATE; DISTEARDIMONIUM HECTORITE; MADECASSOSIDE; 1,2-HEXANEDIOL; PEG-10 DIMETHICONE (200 CST); HYDROXYACETOPHENONE; SODIUM HYDROXIDE

84558-007

Active Ingredient(s)

Zinc Oxide 2.85%
Titanium Dioxide 2.76%
EthylhexyI Salicylate 5%
Phenylbenzimidazole Sulfonic Acid 3.2%

Purpose

Sunscreen

Use

● Helps prevent sunburn.
● Ifused as directed with other sun protection measures (see Directions), decreases the risk of skin
cancer and early skin aging caused by the sun.

Warnings

For external use only

Do not use on damaged or broken skin

When using this product keep out of eyes. Rinse with water to remove

Stop use and ask a doctor if rash occurs

Keep out of reach of children. If swallowed, get medical help or contact a Poison Control Center right away

Directions

●Apply liberally 15 minutes before sun exposure.

●Children under 6 months of age : Ask a doctor.
●Reapply at least every 2 hours, and after 40 minutes of swimming or sweating.
●Sun Protection Measures. Spending time in the sun increases your risk of skin cancer and early skin aging. To decrease this risk, regularly use a sunscreen with a Broad Spectrum SPF of 15 or higher and other sun protection measures including:
●limit time in the sun, especially from10 a.m.-2 p.m.
●wear long-sleeve shirts, pants, hats, and sunglasses

Other information

●Protect the product in this container from excessive heat and direct sun.
●Sun alert : Limiting sun exposure, wearing protective clothing, and using sunscreens may reduce the
risks of skin aging, skin cancer, and other harmful effects of the sun.

Inactive ingredients

Aqua, Glycerin, Silica, Butylene Glycol, Neopenty|l Gly-col Diheptanoate, Cyclopentasiloxane, Isohexadecane,
Cety| Peg/Ppg-10/1 Dimethicone, C12-15 AlkyI Benzo-ate, Cyclohexasiloxane, Niacinamide, Magnesium Sul-
fate, Disteardimonium Hectorite, Madecassoside,1,2-Hexanediol, Peg-10 Dimethicone, Sorbitan Sesqui-
oleate, Hydroxyacetophenone, Sodium Hydroxide,